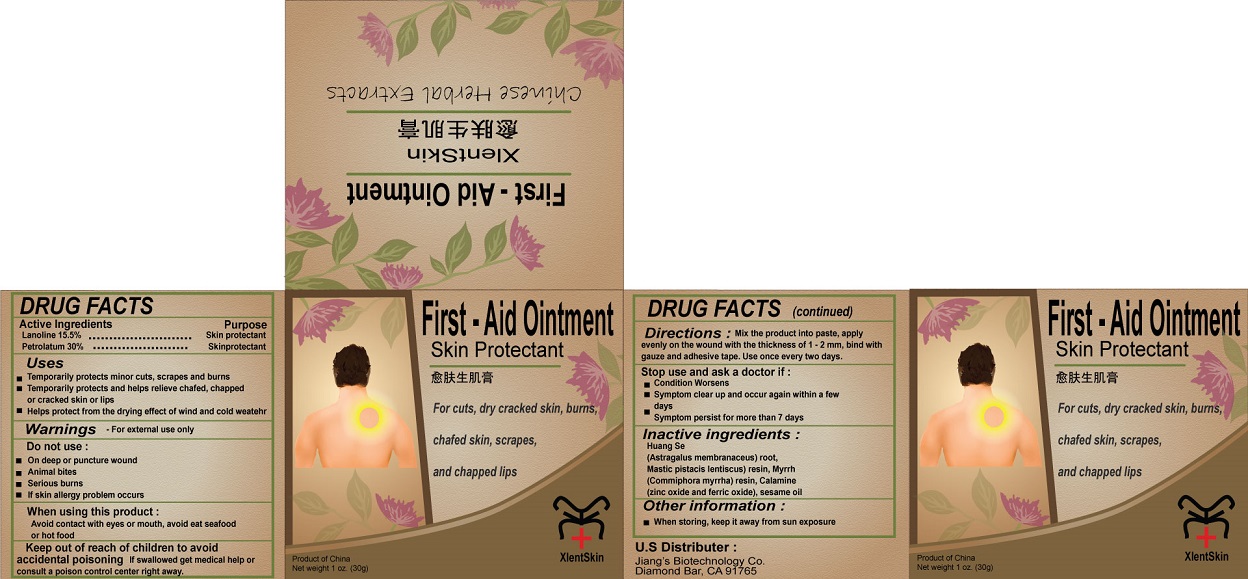 DRUG LABEL: XlentSkin
NDC: 71649-3776 | Form: OINTMENT
Manufacturer: Jiangsu Jiang Shi Biological Technology Co., Ltd.
Category: otc | Type: HUMAN OTC DRUG LABEL
Date: 20220216

ACTIVE INGREDIENTS: LANOLIN 15.5 g/100 g; PETROLATUM 30 g/100 g
INACTIVE INGREDIENTS: ASTRAGALUS PROPINQUUS ROOT; PISTACIA LENTISCUS RESIN; MYRRH; ZINC OXIDE; FERRIC OXIDE RED; SESAME OIL

XlentSkin

Active Ingredients

Lanolin 15.5%

Petrolatum 30%

Purpose

Skin protectant

Uses

• Temporarily protects minor cuts, scrapes and burns

• Temporarily protects and helps relieve chafed, chapped or cracked skin or lips

• Helps protect from the drying effect of wind and cold weather

Warnings - For external use only

Do not use :
• On deep or puncture wound
• Animal bites
• Serious burns
• If skin allergy problem occurs

When using this product :
Avoid contact with eyes or mouth, avoid eat seafood or hot food

Stop use and ask a doctor if :
• Condition Worsens
• Symptom clear up and occur again within a few days
• Symptom persist for more than 7 days

Keep out of reach of children to avoid accidental poisoning If swallowed get medical help or consult a poison control center right away.

DOSAGE AND ADMINISTRATION

Directions: Mix the product into paste, apply evenly on the wound with the thickness of 1 -2 mm, bind with gauze and adhesive tape. Use once every two days.

Inactive ingredients :

Huang Se (Astragalus membranaceus) root, Mastic pistacis lentiscus) resin, Myrrh (Commiphora myrrha) resin, Calamine (zinc oxide and ferric oxide), sesame oil

Other information :

• When storing, keep it away from sun exposure

First – Aid Ointment
Skin Protectant
For cuts, dry cracked skin, burns, chafed skin, scrapes, and chapped lips
Product of China
U.S Distributer :
Jiang’s Biotechnology Co. Diamond Bar, CA 91765